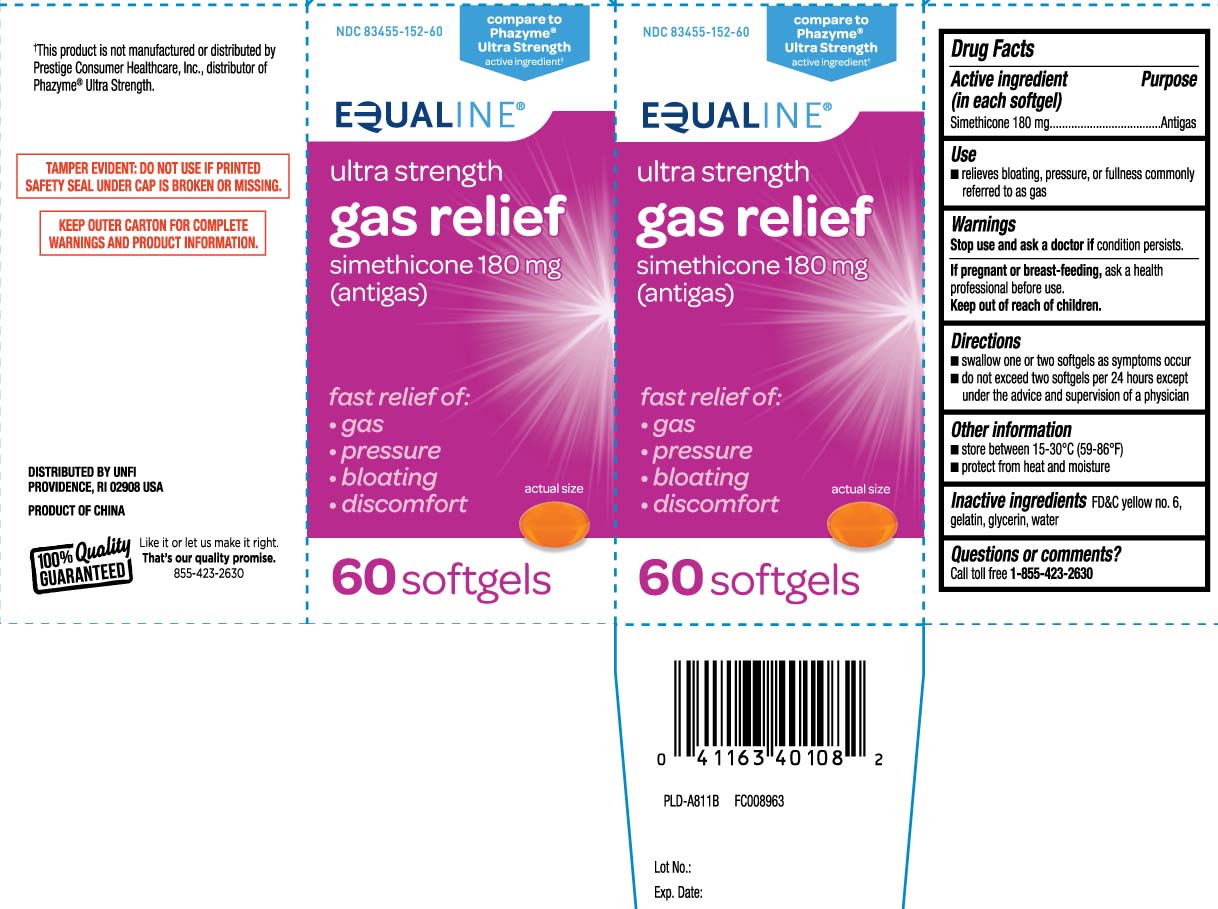 DRUG LABEL: Gas Relief
NDC: 83455-152 | Form: CAPSULE, LIQUID FILLED
Manufacturer: United Natural Foods, Inc. dba UNFI
Category: otc | Type: HUMAN OTC DRUG LABEL
Date: 20251007

ACTIVE INGREDIENTS: DIMETHICONE 180 mg/1 1
INACTIVE INGREDIENTS: FD&C YELLOW NO. 6; GELATIN; GLYCERIN; WATER; FD&C RED NO. 40

Drug Facts

Active ingredient (in each softgel)

Simethicone 180 mg

Purpose

Antigas

Uses

- relieves bloating, pressure, or fullness commonly referred to as gas

Warnings

Stop use and ask a doctor if

condition persists.

If pregnant or breast-feeding,

ask a health professional before use.

Directions

- swalow one or two softgels as needed after a meal
- do not exceed two softgels per 24 hours except under the advice and supervision of a physician

Other information

- store at 15º-30ºC (59º-86ºF)
- protect from heat and moisture

Inactive ingredients

FD&C yellow #6, gelatin, glycerin, purified water

Questions or comments?

Call toll free 1-855-423-2630

Principal Display Panel

*Compare to Phazyme® Ultra Strength active ingredient†

Ultra Strength

gas relief

simethicone 180 mg

(Antigas)

Fast relief of:

- gas
- pressure
- bloating
- discomfort

Softgels

†This product is not manufactured or distributed by Prestige Consumer Healthcare, Inc., distributor of Phazyme® Ultra Strength.

TAMPER EVIDENT: DO NOT USE IF PRINTED SAFETY SEAL UNDER CAP IS BROKEN OR MISSING.

KEEP OUTER CARTON FOR COMPLETE WARNINGS AND PRODUCT INFORMATION.

DISTRIBUTED BY UNFI

PROVIDENCE, RI 02908

Product Label

EQUALINE Ultra Strength GasRelief